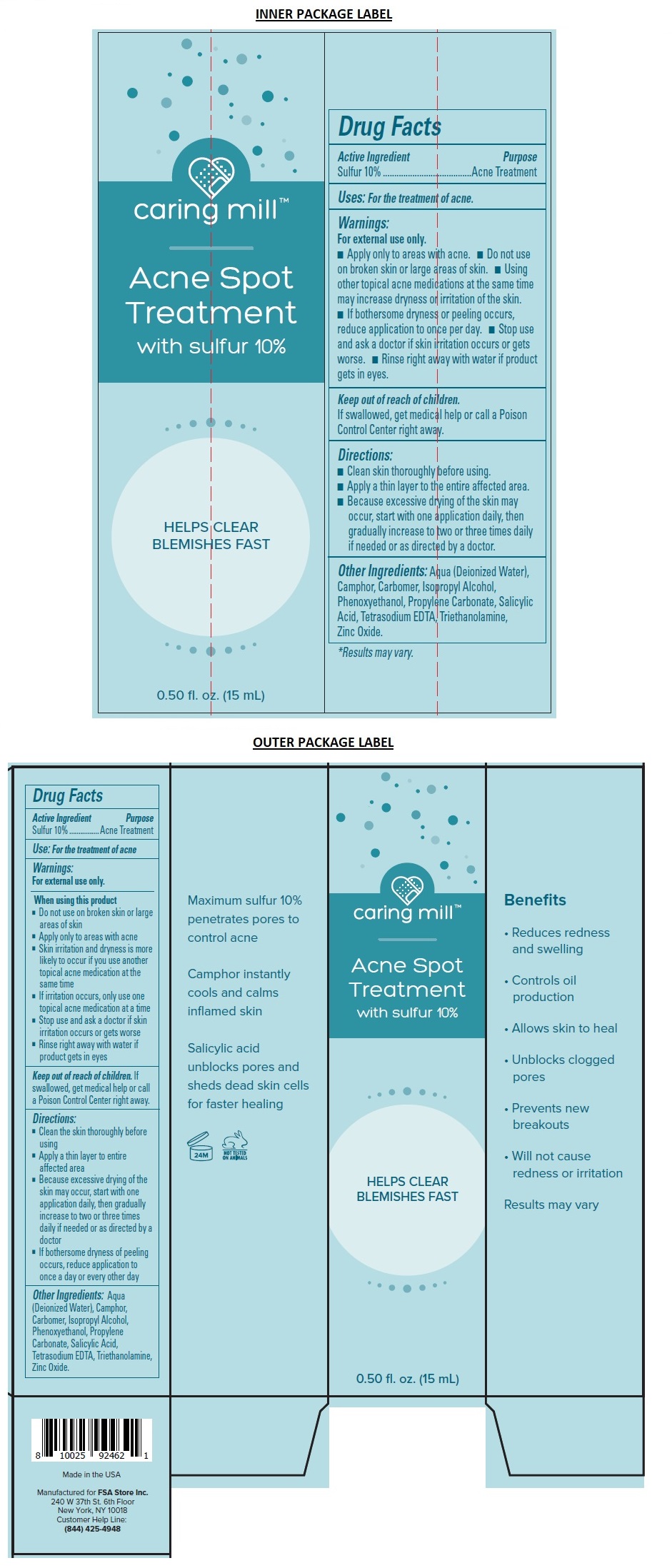 DRUG LABEL: caring mill Acne Spot Treatment
NDC: 71328-062 | Form: CREAM
Manufacturer: Clixit, Llc
Category: otc | Type: HUMAN OTC DRUG LABEL
Date: 20210621

ACTIVE INGREDIENTS: SULFUR 100 mg/1 mL
INACTIVE INGREDIENTS: WATER; CAMPHOR (SYNTHETIC); CARBOMER HOMOPOLYMER TYPE C (ALLYL PENTAERYTHRITOL CROSSLINKED); ISOPROPYL ALCOHOL; PHENOXYETHANOL; PROPYLENE CARBONATE; SALICYLIC ACID; EDETATE SODIUM; TROLAMINE; ZINC OXIDE

caring mill™ Acne Spot Treatment

Active Ingredient

Sulfur 10%

Purpose

Acne Treatment

Use:

For the treatment of acne

Warnings:

For external use only.

When using this product
• Do not use on broken skin or large areas of skin
• Apply only to areas with acne
• Skin irritation and dryness is more likely to occur if you use another topical acne medication at the same time
• If irritation occurs, only use one topical acne medication at a time
• Stop use and ask a doctor if skin irritation occurs or gets worse
• Rinse right away with water if product gets in eyes

Keep out of reach of children. If swallowed, get medical help or call a Poison Control Center right away.

Directions:

• Clean the skin thoroughly before using
• Apply a thin layer to entire affected area
• Because excessive drying of the skin may occur, start with one application daily, then gradually increase to two or three times daily if needed or as directed by a doctor
• If bothersome dryness of peeling occurs, reduce application to once a day or every other day

Other Ingredients:

Aqua (Deionized Water), Camphor, Carbomer, Isopropyl Alcohol, Phenoxyethanol, Propylene Carbonate, Salicylic Acid, Tetrasodium EDTA, Triethanolamine, Zinc Oxide.

HELPS CLEAR BLEMISHES FAST

Benefits

• Reduces redness and swelling

• Controls oil production

• Allows skin to heal

• Unblocks clogged pores

• Prevents new breakouts

• Will not cause redness or irritation

Results may vary

Maximum sulfur 10% penetrates pores to control acne

Camphor instantly cools and calms inflamed skin

Salicylic acid unblocks pores and sheds dead skin cells for faster healing

NOT TESTED ON ANIMALS

Made in the USA

Manufactured for FSA Store Inc.
240 W 37th St. 6th Floor
New York, NY 10018
Customer Help Line:
(844) 425-4948